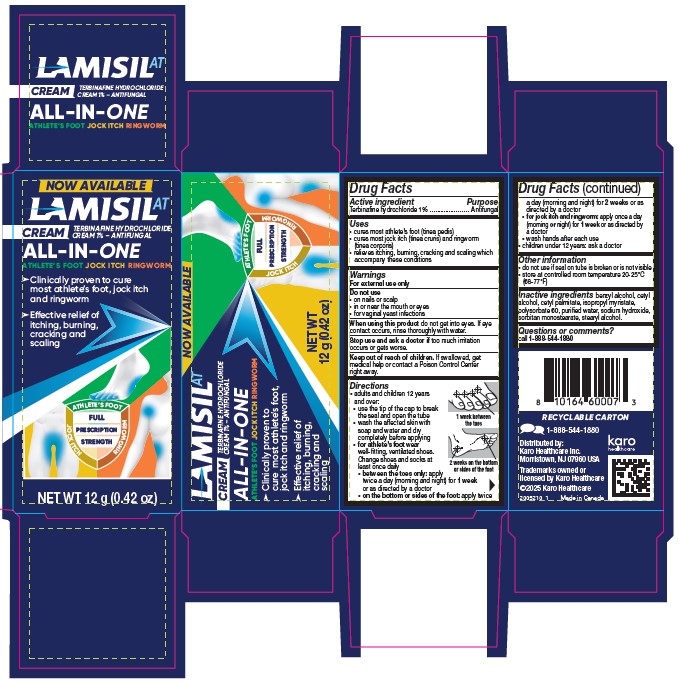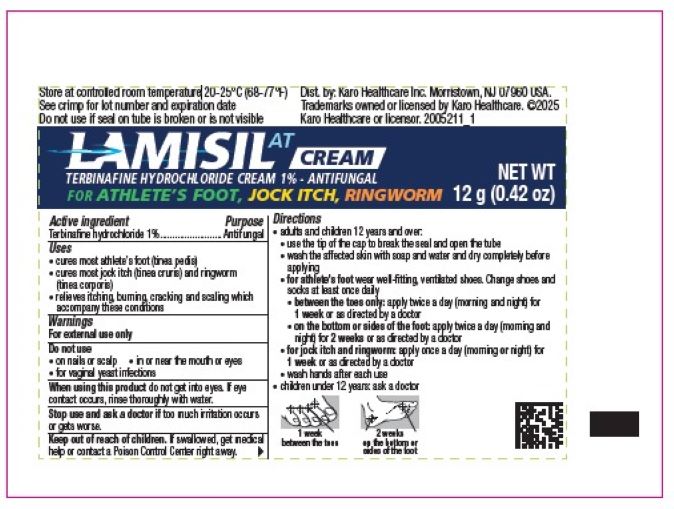 DRUG LABEL: Lamisil AT Cream
NDC: 84485-4030 | Form: CREAM
Manufacturer: Karo Healthcare Inc.
Category: otc | Type: HUMAN OTC DRUG LABEL
Date: 20251002

ACTIVE INGREDIENTS: TERBINAFINE HYDROCHLORIDE 1 g/100 g
INACTIVE INGREDIENTS: CETYL ALCOHOL; POLYSORBATE 60; STEARYL ALCOHOL; BENZYL ALCOHOL; CETYL PALMITATE; ISOPROPYL MYRISTATE; WATER; SODIUM HYDROXIDE; SORBITAN MONOSTEARATE

Lamisil AT (Terbinafine Hydrochloride) Cream 1% 12 g

Active Ingredient

Terbinafine hydrochloride 1%

Purpose

Antifungal

Uses

- cures most athlete's foot (tinea pedis)
- cures most jock itch (tinea cruris) and ringworm (tinea corporis)
- relieves itching, burning, cracking and scaling which accompany these conditions

Warnings

For external use only

Do not use

- on nails or scalp
- in or near the mouth or eyes
- for vaginal yeast infections

When using this product do not get into eyes. If eye contact occurs, rinse thoroughly with water.

Stop use and ask a doctor if too much irritation occurs or gets worse

Keep out of reach of children. If swallowed, get medical help or contact a Poison Control Center right away.

Directions

- adults and children 12 years and over:
  - use the tip of the cap to break the seal and open the tube
  - wash the affected skin with soap and water and dry completely before applying
  - for athlete's foot wear well-fitting, ventilated shoes. Change shoes and socks at least once daily.
    - between the toes only: apply twice a day (morning and night) for 1 week or as directed by a doctor
    - on the bottom or sides of the foot: apply twice a day (morning and night) for 2 weeks or as directed by a doctor
  - for jock itch and ringworm: apply once a day (morning or night) for 1 week or as directed by a doctor
  - wash hands after each use
- children under 12 years: ask a doctor

Other Information

- do no use if seal on tube is broken or is not visible
- store at controlled room temperature 20-25°C (68-77°F)

Inactive Ingredients

benzyl alcohol, cetyl alcohol, cetyl palmitate, isopropyl myristate, polysorbate 60, purified water, sodium hydroxide, sorbitan monostearate, stearyl alcohol

Questions or comments?

call 1-888-544-1880

PACKAGE LABEL.PRINCIPAL DISPLAY

LAMISILAT
CREAM
TERBINAFINE HYDROCHLORIDE
CREAM 1% - ANTIFUNGAL
ALL-IN-ONE

ATHLETE'S FOOT, JOCK ITCH, RINGWORM
►Clinically proven to cure most athlete’s foot, jock itch and ringworm
► Effective relief of itching, burning, cracking and scaling
► FULL PRESCRIPTION STRENGTH
NET WT 12 g (0.42 oz)
RECYCLABLE CARTON
1-888-544-1880
Distributed By:
Karo Healthcare Inc.
Morristown, NJ 07960 USA
Trademarks owned or
licensed By Karo Healthcare
©2025 Karo Healthcare
2005210_1 Made in Canada

LAMISILAT CREAM
TERBINAFINE HYDROCHLORIDE CREAM 1% - ANTIFUNGAL
FOR ATHLETE'S FOOT, JOCK ITCH, RINGWORM
NET WT
12g (0.42 oz)
2005211_1